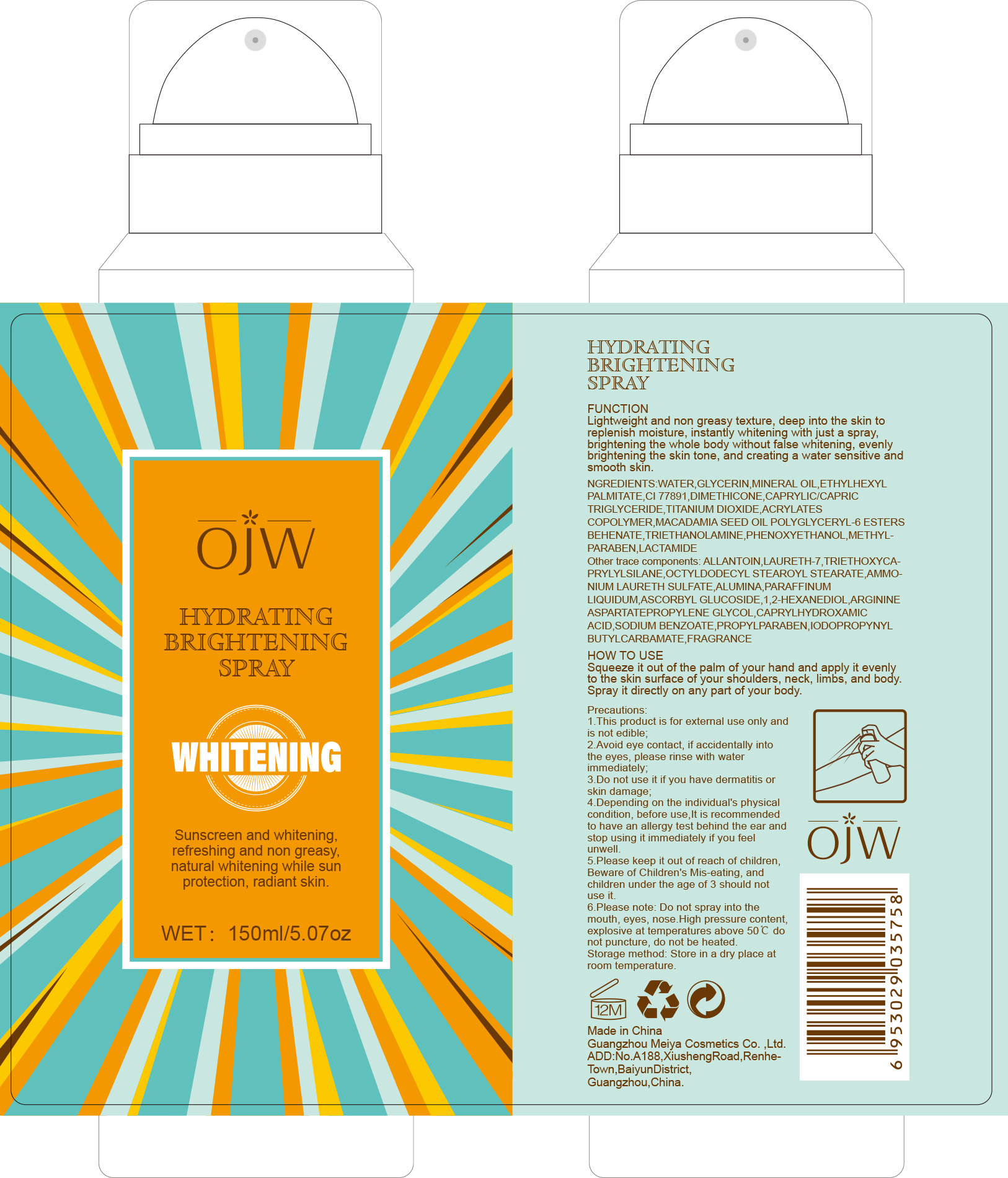 DRUG LABEL: Brightening
NDC: 84673-010 | Form: EMULSION
Manufacturer: Guangzhou Meiya Cosmetics Co. ,Ltd.
Category: otc | Type: HUMAN OTC DRUG LABEL
Date: 20240927

ACTIVE INGREDIENTS: ASCORBYL GLUCOSIDE 150 mg/1 mL
INACTIVE INGREDIENTS: MINERAL OIL 5.1 mg/1 mL; LACTAMIDE 0.192 mg/1 mL; TRIETHOXYCAPRYLYLSILANE 0.02 mg/1 mL; DIMETHICONE 1 mg/1 mL; PHENOXYETHANOL 0.294 mg/1 mL; CAPRYLHYDROXAMIC ACID 0.0008 mg/1 mL; IODOPROPYNYL BUTYLCARBAMATE 0.006 mg/1 mL; TITANIUM DIOXIDE 0.679 mg/1 mL; WATER 73.86 mg/1 mL; LAURETH-7 0.05 mg/1 mL; ARGININE ASPARTATE 0.002 mg/1 mL; GLYCERIN 8 mg/1 mL; ETHYLHEXYL PALMITATE 4 mg/1 mL; OCTYLDODECYL STEAROYL STEARATE 0.032 mg/1 mL; PROPYLPARABEN 0.1 mg/1 mL; SODIUM BENZOATE 0.0125 mg/1 mL; 1,2-HEXANEDIOL 0.0056 mg/1 mL; METHYLPARABEN 0.2 mg/1 mL; ALLANTOIN 0.1 mg/1 mL

PURPOSE

Function: Lightweight and non greasy texture, deep into the skin to replenish moisture, instantly whitening with just a spray, brightening the whole body without false whitening, evenly brightening the skin tone, and creating a water sensitive and smooth skin.

INDICATIONS AND USAGE

How to use: Squeeze it out of the palm of your hand and apply it evenly to the skin surface of your shoulders, neck, limbs, and body. Spray it directly on any part of your body.

WARNINGS

1. This product is for external use only and is not edible;

2. Avoid eye contact, if accidentally into the eyes, please rinse with water immediately;

3. Do not use it if you have dermatitis or skin damage;

4. Depending on the individual's physical condition, before use,It is recommended to have an allergy test behind the ear and stop using it immediately if you feel unwell.

5. Please keep it out of reach of children, Beware of Children's Mis-eating, and children under the age of 3 should not use it.

6.Please note: Do not spray into the mouth, eyes, nose.High pressure content, explosive at temperatures above 50℃ do not puncture, do not be heated.

STOP USE

1. Avoid eye contact, if accidentally into the eyes, please rinse with water immediately;

2. Do not use it if you have dermatitis or skin damage;

3. Depending on the individual's physical condition, before use,It is recommended to have an allergy test behind the ear and stop using it immediately if you feel unwell.

DO NOT USE

1. Do not use it if you have dermatitis or skin damage;

2. Depending on the individual's physical condition, before use,It is recommended to have an allergy test behind the ear and stop using it immediately if you feel unwell.

WHEN USING

1. This product is for external use only and is not edible;

2. Avoid eye contact, if accidentally into the eyes, please rinse with water immediately;

3. Do not use it if you have dermatitis or skin damage;

4. Depending on the individual's physical condition, before use,It is recommended to have an allergy test behind the ear and stop using it immediately if you feel unwell.

5. Please keep it out of reach of children, Beware of Children's Mis-eating, and children under the age of 3 should not use it.

6.Please note: Do not spray into the mouth, eyes, nose.High pressure content, explosive at temperatures above 50℃ do not puncture, do not be heated.

KEEP OUT OF REACH OF CHILDREN

Please keep it out of reach of children, Beware of Children's Mis-eating, and children under the age of 3 should not use it.